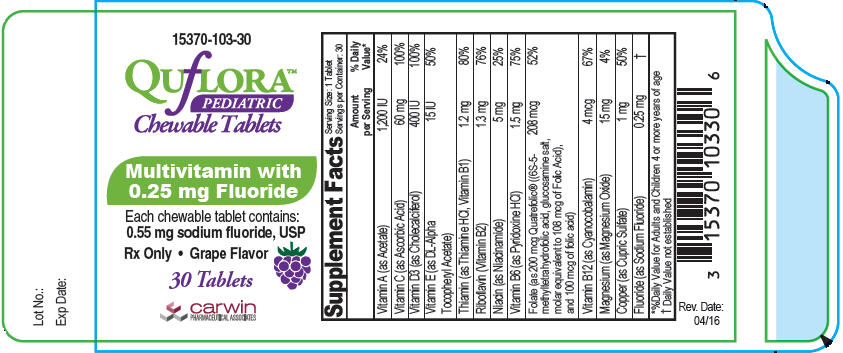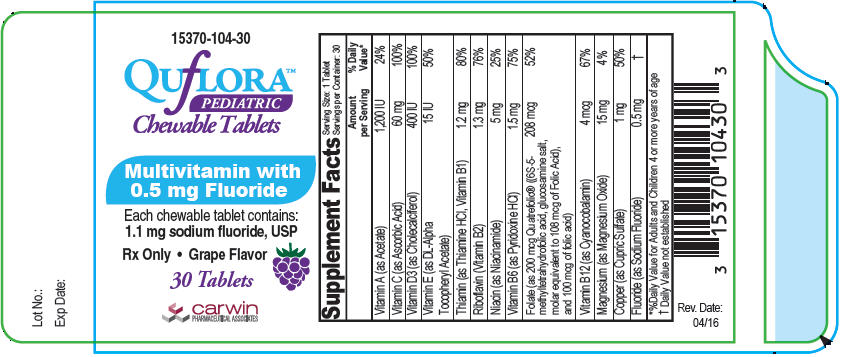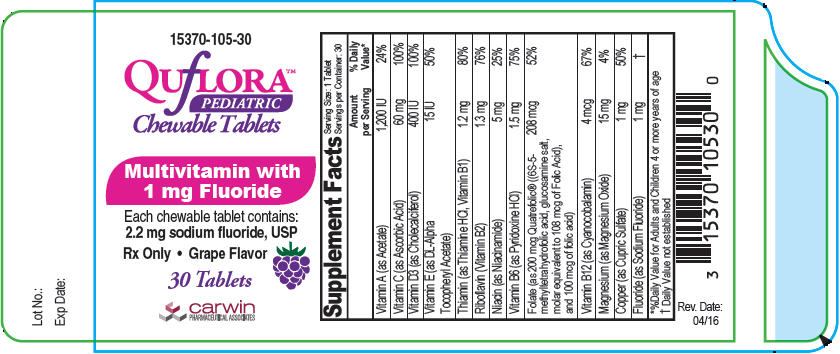 DRUG LABEL: Quflora Pediatric
NDC: 15370-103 | Form: TABLET, CHEWABLE
Manufacturer: CarWin Pharmaceutical Associates, LLC
Category: prescription | Type: HUMAN PRESCRIPTION DRUG LABEL
Date: 20240110

ACTIVE INGREDIENTS: VITAMIN A ACETATE 1200 [iU]/1 1; ASCORBIC ACID 60 mg/1 1; CHOLECALCIFEROL 400 [iU]/1 1; .ALPHA.-TOCOPHEROL, DL- 15 [iU]/1 1; THIAMINE HYDROCHLORIDE 1.2 mg/1 1; RIBOFLAVIN 1.3 mg/1 1; NIACINAMIDE 5 mg/1 1; PYRIDOXINE HYDROCHLORIDE 1.5 mg/1 1; LEVOMEFOLIC ACID 108 ug/1 1; FOLIC ACID 100 ug/1 1; CYANOCOBALAMIN 4 ug/1 1; MAGNESIUM OXIDE 15 mg/1 1; CUPRIC SULFATE 1 mg/1 1; SODIUM FLUORIDE 0.25 mg/1 1
INACTIVE INGREDIENTS: GRAPE; CITRIC ACID MONOHYDRATE; SILICON DIOXIDE; MAGNESIUM STEARATE; MICROCRYSTALLINE CELLULOSE; SUCRALOSE; SUCROSE; STEARIC ACID

Quflora™ Pediatric Chewable Tablets

Supplement Facts
Serving Size: 1 Tablet
Servings per Container: 30
 | Amount per Serving | % Daily Value [%Daily Value for Adults and Children 4 or more years of age]
Vitamin A (as Acetate) | 1,200 IU | 24%
Vitamin C (as Ascorbic Acid) | 60 mg | 100%
Vitamin D3 (as Cholecalciferol) | 400 IU | 100%
Vitamin E (as DL-Alpha Tocopheryl Acetate) | 15 IU | 50%
Thiamin (as Thiamine HCl, Vitamin B1) | 1.2 mg | 80%
Riboflavin (Vitamin B2) | 1.3 mg | 76%
Niacin (as Niacinamide) | 5 mg | 25%
Vitamin B6 (as Pyridoxine HCl) | 1.5 mg | 75%
Folate (as 200 mcg Quatrefolic® ((6S-5-methyltetrahydrofolic acid, glucosamine salt, molar equivalent to 108 mcg of Folic Acid), and 100 mcg of folic acid) | 208 mcg | 52%
Vitamin B12 (as Cyanocobalamin) | 4 mcg | 67%
Magnesium (as Magnesium Oxide) | 15 mg | 4%
Copper (as Cupric Sulfate) | 1 mg | 50%
Fluoride (as Sodium Fluoride) | 0.5 mg | [Daily Value not established]

Other Ingredients: Citric acid, fumed silica, magnesium stearate, microcrystalline cellulose, natural grape flavor, silicon dioxide, stearic acid, sucralose, sucrose and xylitol.

INDICATIONS AND USAGE

Quflora™ Pediatric Chewable Tablets with 0.5 mg Fluoride is a prescription dietary fluoride supplement providing twelve essential vitamins and minerals.

CONTRAINDICATIONS

Quflora™ Pediatric Chewable Tablets with 0.5 mg Fluoride should not be used by patients with a known history of hypersensitivity to any of the listed ingredients.

PRECAUTIONS

General

The suggested dose should not be exceeded, since dental fluorosis may result from continued ingestion of large amounts of fluoride. Do not eat or drink dairy products within one hour of fluoride administration. Incompatibility of fluoride with dairy foods has been reported due to formation of calcium fluoride which is poorly absorbed. Your healthcare practitioner can prescribe the correct dosage.

Folic Acid

Folic Acid alone is improper therapy in the treatment of pernicious anemia and other megaloblastic anemias where vitamin B12 is deficient. Folic acid in doses above 0.1 mg daily may obscure pernicious anemia in that hematologic remission can occur while neurological manifestations progress.

ADVERSE REACTIONS

Allergic rash and other idiosyncrasies have been rarely reported. Call your doctor for medical advice about side effects. You may report side effects or obtain product information by calling Carwin Pharmaceutical Associates, LLC at 1-844-700-5011.

WARNINGS

Keep out of the reach of children. In case of accidental overdose, seek professional emergency assistance or contact a Poison Control Center immediately. This product should be chewed and is not recommended for children under age 4.

DOSAGE AND ADMINISTRATION

One tablet daily or as prescribed by your healthcare practitioner. Each tablet contains 0.5 mg fluoride ion (F) from 1.1 mg sodium fluoride (NaF).

DESCRIPTION

Quflora™ Pediatric Chewable Tablets with 0.5 mg Fluoride is a yellow round tablet imprinted "104".

HOW SUPPLIED

Quflora™ Pediatric Chewable Tablets with 0.5 mg Fluoride available in child-resistant bottles of 30 (Product Code: 15370-104-30).

Rx Only

STORAGE

Store at controlled room temperature 20° C to 25° C (68° F to 77° F), excursions permitted between 15° C and 30° C (59° F and 86° F). Protect from light, moisture and excessive heat.

KEEP THIS PRODUCT OUT OF REACH OF CHILDREN.

TAMPER EVIDENT

Do not use if seal is broken or missing.

Quatrefolic® is a registered trademark of Gnosis, SpA. Covered by one or more claims of U.S. Patent # 7,947,662 CAS# 1181972-37-1

Manufactured for:
Carwin Pharmaceutical Associates, LLC
Hazlet, NJ 07730
www.carwinpharma.com

Made in Canada

Rev. 4/16

PRINCIPAL DISPLAY PANEL - 0.25 mg Tablet Bottle Label

15370-103-30

QUfLORA™
PEDIATRIC
Chewable Tablets

Multivitamin with
0.25 mg Fluoride

Each chewable tablet contains:
0.55 mg sodium fluoride, USP

Rx Only • Grape Flavor

30 Tablets

carwin
PHARMACEUTICAL ASSOCIATES

PRINCIPAL DISPLAY PANEL - 0.5 mg Tablet Bottle Label

15370-104-30

QUfLORA™
PEDIATRIC
Chewable Tablets

Multivitamin with
0.5 mg Fluoride

Each chewable tablet contains:
1.1 mg sodium fluoride, USP

Rx Only • Grape Flavor

30 Tablets

carwin
PHARMACEUTICAL ASSOCIATES

PRINCIPAL DISPLAY PANEL - 1 mg Tablet Bottle Label

15370-105-30

QUfLORA™
PEDIATRIC
Chewable Tablets

Multivitamin with
1 mg Fluoride

Each chewable tablet contains:
2.2 mg sodium fluoride, USP

Rx Only • Grape Flavor

30 Tablets

carwin
PHARMACEUTICAL ASSOCIATES